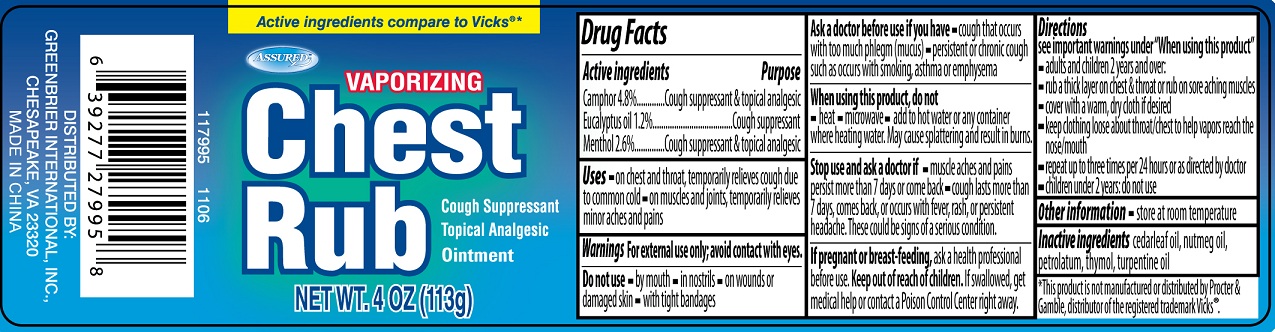 DRUG LABEL: Assured Vaporizing Chest Rub
NDC: 33992-7995 | Form: OINTMENT
Manufacturer: Greenbrier International, Inc.
Category: otc | Type: HUMAN OTC DRUG LABEL
Date: 20110706

ACTIVE INGREDIENTS: CAMPHOR (SYNTHETIC) 4.8 g/100 g; MENTHOL 2.6 g/100 g; EUCALYPTUS OIL 1.2 g/100 g
INACTIVE INGREDIENTS: CEDAR LEAF OIL; NUTMEG OIL; PETROLATUM; THYMOL; TURPENTINE

Assured Vaporizing Chest Rub

Active Ingredient

Camphor 4.8%

Eucalyptus Oil 1.2%

Menthol 2.6%

Purpose

Cough Suppressant and Topical analgesic

Cough Suppressant

Cough Suppressant and Topical Analgesic.

Uses

on chest and throat, temporarily relieves cough due to common cold

on muscles and joints, temporarily relieves minor aches and pains.

Warnings

For external use only; avoid contact with eyes.

Do not use

by mouth

in nostrils

on wounds or damaged skin

with tight bandages

Ask doctor before use if you have cough that occurs with too much phlegm (mucus)

persistent or chronic cough such as occurs with smoking, asthma or emphysema.

When using this product, do not

heat, microwave, add hot water or any container where heating water may cause splattering and result in burns.

Stop use and ask a doctor if

muscle aches and pains persist more than 7 days or come back

cough lasts more than 7 days, comes back, or occurs with fever, rash or persistent headache.

These could be signs of a serious condition.

If pregnant or breast-feeding,

ask a health professional before use

Keep out of reach of children.

If swallowed, get medical help or contact a Poison Control Center right away.

Directions

see important warnings under "When using this product"

adults and children 2 years and over:

rub a thick layer on chest and throat or rub on sore aching muscles

cover with a warm, dry cloth if desired

keep clothing loose about throat/chest to help vapors reach the nose/mouth

repeat up to three times per 24hours or as directed by doctor

children under 2 years do not use.

Other information

store at room temperature

INACTIVE INGREDIENT

cedarleaf oil, nutmeg oil, petrolatum, thymol, turpentine oil

*This product is not manufactured or distributed by Procter and Gamble, distributor of the registered trademark Vicks(r).

PACKAGE LABEL

Vaporizing Chest Rub

Cough Suppressant

Topical Analgesic

Ointment

NET WT 4OZ (113g)

DISTRIBUTED BY

GREENBRIER INTERNATIONAL, INC.

CHESAPEAKE, VA 23320

MADE IN CHINA